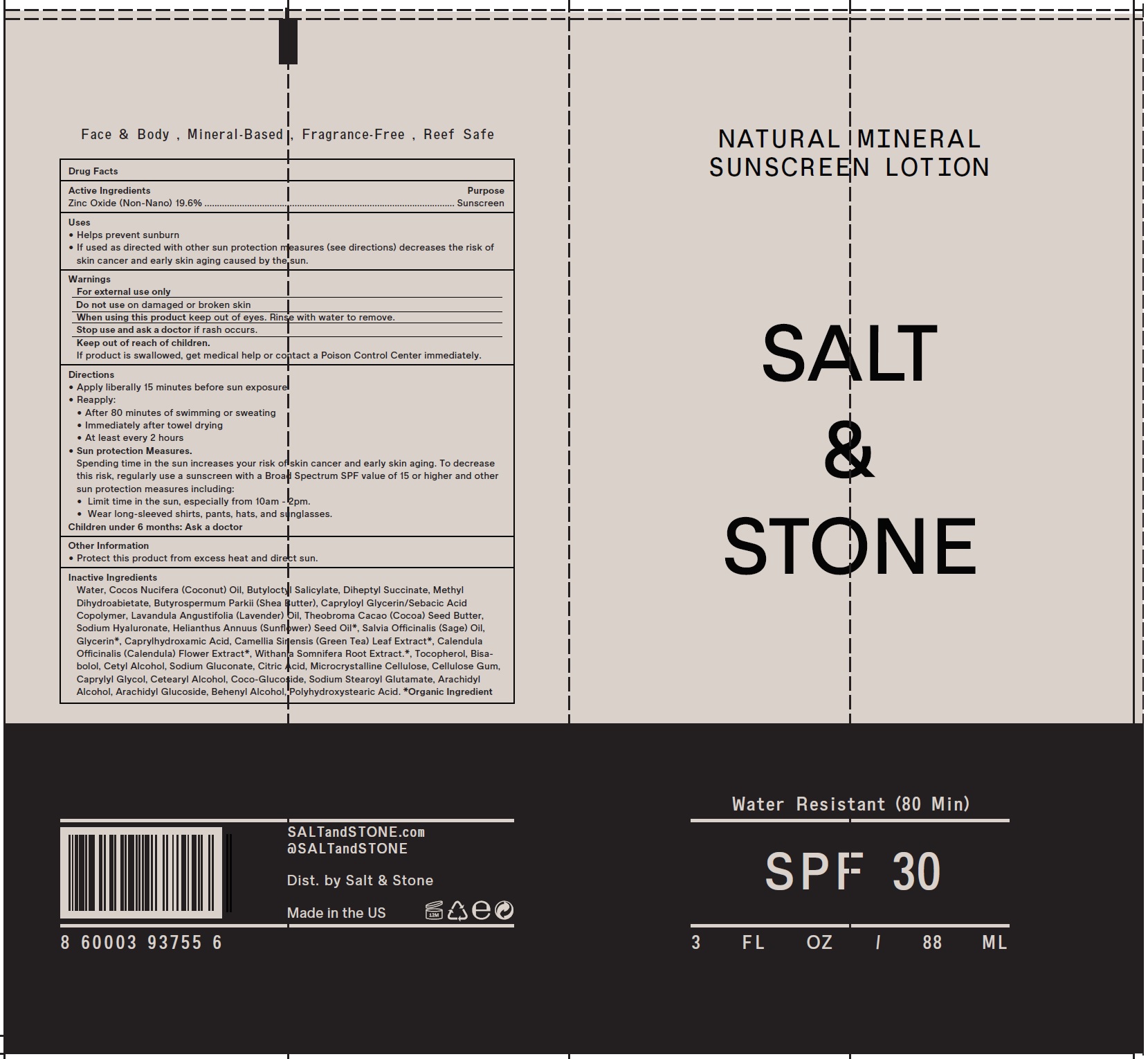 DRUG LABEL: Salt and Stone Natural Mineral Sunscreen  SPF 30
NDC: 71585-136 | Form: LOTION
Manufacturer: Salt and Stone LLC
Category: otc | Type: HUMAN OTC DRUG LABEL
Date: 20231028

ACTIVE INGREDIENTS: ZINC OXIDE 196 mg/1 mL
INACTIVE INGREDIENTS: WATER; COCONUT OIL; BUTYLOCTYL SALICYLATE; DIHEPTYL SUCCINATE; METHYL DIHYDROABIETATE; SHEA BUTTER; CAPRYLOYL GLYCERIN/SEBACIC ACID COPOLYMER (2000 MPA.S); LAVENDER OIL; COCOA BUTTER; HYALURONATE SODIUM; SUNFLOWER OIL; SAGE OIL; GLYCERIN; CAPRYLHYDROXAMIC ACID; GREEN TEA LEAF; CALENDULA OFFICINALIS FLOWER; WITHANIA SOMNIFERA ROOT; TOCOPHEROL; LEVOMENOL; CETYL ALCOHOL; SODIUM GLUCONATE; CITRIC ACID MONOHYDRATE; MICROCRYSTALLINE CELLULOSE; CARBOXYMETHYLCELLULOSE SODIUM, UNSPECIFIED; CAPRYLYL GLYCOL; CETOSTEARYL ALCOHOL; COCO GLUCOSIDE; SODIUM STEAROYL GLUTAMATE; ARACHIDYL ALCOHOL; ARACHIDYL GLUCOSIDE; DOCOSANOL

Salt & Stone Natural Mineral Sunscreen Lotion SPF 30, 3 fl.Oz.(88 mL)

Active Ingredients

Zinc Oxide (Non-Nano) 19.6%

Purpose

Sunscreen

Uses

• Helps prevent sunburn • If used as directed with other sun protection measures (see directions) decreases the risk of skin cancer and early skin aging caused by the sun.

Warnings

For external use only

on damaged or broken skin Do not use

WHEN USING

keep out of eyes. Rinse with water to remove. When using this product

STOP USE

if rash occurs. Stop use and ask a doctor

Keep out of reach of children.

If product is swallowed, get medical help or contact a Poison Control Center immediately.

Directions

• Apply liberally 15 minutes before sun exposure • Reapply: • After 80 minutes of swimming or sweating • Immediately after towel drying • At least every 2 hours • . Spending time in the sun increases your risk of skin cancer and early skin aging. To decrease this risk, regularly use a sunscreen with a Broad Spectrum SPF value of 15 or higher and other sun protection measures including: • Limit time in the sun, especially from 10am - 2pm. • Wear long-sleeved shirts, pants, hats, and sunglasses.
Sun protection Measures

- Children under 6 months: Ask a doctor

Other Information

• Protect this product from excess heat and direct sun.

Inactive Ingredients

Water, Cocos Nucifera (Coconut) Oil, Butyloctyl Salicylate, Diheptyl Succinate, Methyl Dihydroabietate, Butyrospermum Parkii (Shea Butter), Capryloyl Glycerin/Sebacic Acid Copolymer, Lavandula Angustifolia (Lavender) Oil, Theobroma Cacao (Cocoa) Seed Butter, Sodium Hyaluronate, Helianthus Annuus (Sunflower) Seed Oil*, Salvia Officinalis (Sage) Oil, Glycerin*, Caprylhydroxamic Acid, Camellia Sinensis (Green Tea) Leaf Extract*, Calendula Officinalis (Calendula) Flower Extract*, Withania Somnifera Root Extract.*, Tocopherol, Bisabolol, Cetyl Alcohol, Sodium Gluconate, Citric Acid, Microcrystalline Cellulose, Cellulose Gum, Caprylyl Glycol, Cetearyl Alcohol, Coco-Glucoside, Sodium Stearoyl Glutamate, Arachidyl Alcohol, Arachidyl Glucoside, Behenyl Alcohol, Polyhydroxystearic Acid. *Organic Ingredient